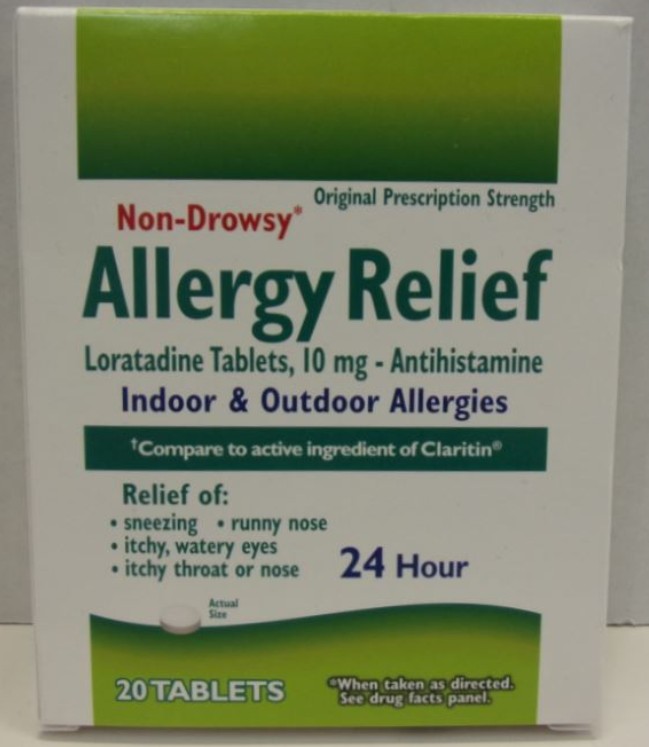 DRUG LABEL: First Aid Direct Allergy Relief
NDC: 42961-120 | Form: TABLET
Manufacturer: Cintas Corporation
Category: otc | Type: HUMAN OTC DRUG LABEL
Date: 20250923

ACTIVE INGREDIENTS: LORATADINE 10 mg/1 1
INACTIVE INGREDIENTS: LACTOSE MONOHYDRATE; MAGNESIUM STEARATE; STARCH, CORN; SODIUM STARCH GLYCOLATE TYPE A

First Aid Direct Allergy Relief

Active Ingredient (in each tablet)

Loratadine 10 mg

Purpose

Antihistamine

Uses

temporatily relieves these symptoms due to hay fever or other upper respiratory allergies:

- runny nose
- itchy, watery eyes
- sneezing
- iching of the nose or throat

Warnings

Do not use

if you have ever had an allergic reaction to this product or any of its ingredients

Ask a doctor before use if you

have liver or kidney disease. Your doctor should determine if you need a different dose.

When using this product

do not take more than directed. Taking more than directed may cause drowsiness.

Stop use and ask a doctor if

an allergic reaction to this product occurs.

Seek medical help right away.

If pregnant or breast-feeding,

ask a health professional before use

Keep out of reach of children.

In case of accidental overdose, contact a doctor or Poison Control Center immediately.

Directions

adults and children 6 years and over | 1 tablet daily; not more than 1 tablet in 24 hours
children under 6 years of age | ask a doctor
consumers with liver or kidney disease | ask a doctor

Other information

- store between 20°C to 25°C (68° to 77°F)
- protect from excessive moisture
- do not use if blister unit is torn or open

Inactive ingredients

lactose monohydrate, magensium stearate, pregelatinized starch, sodium startch glycolate

Questions?

1-800-327-2704 Monday - Friday 8:00am - 5:00pm (CDT)

Principal Display Panel

Original Prescription Strength

Non-Drowsy*

Allergy Relief

Loratadine Tablets, 10 mg - Antihistamine

Indoor & Outdoor Allergies

†Compare to active ingredient of Claritin®

Relief of:

- sneezing
- runny nose
- itchy, watery eyes
- itchy throat or nose

24 Hour

Actual Size

20 TABLETS

*When taken as directed. See drug facts panel